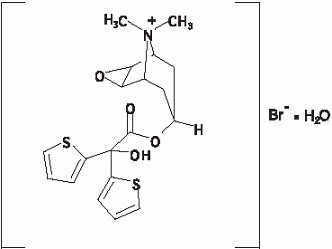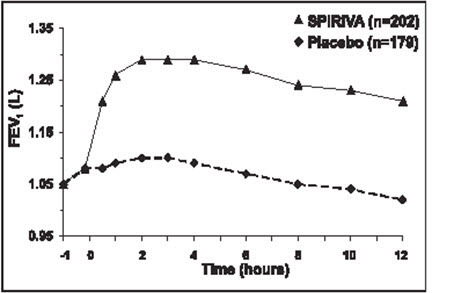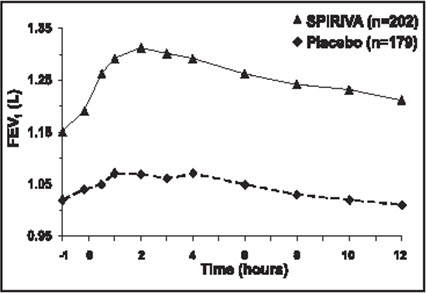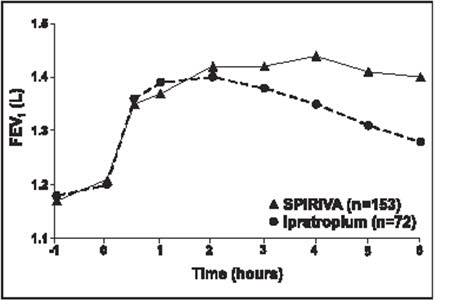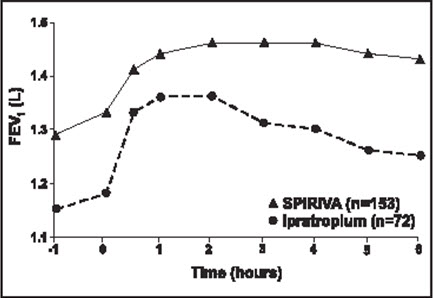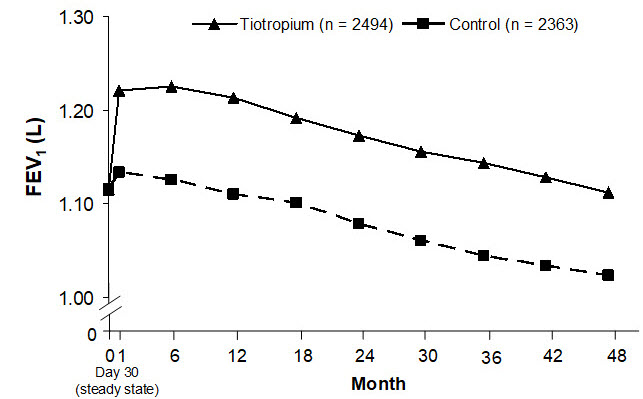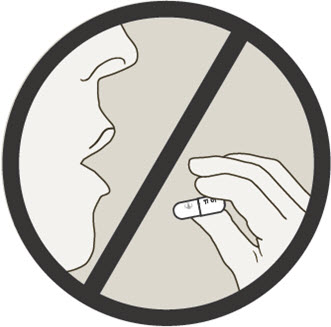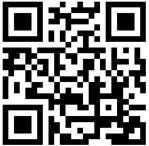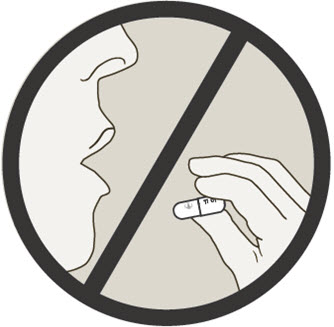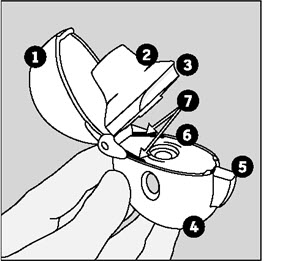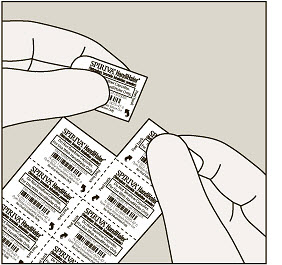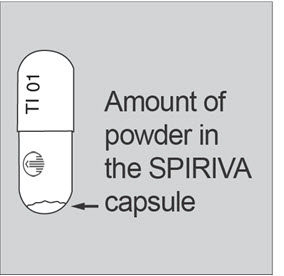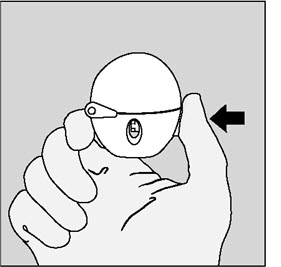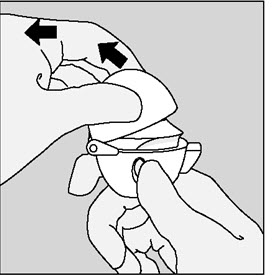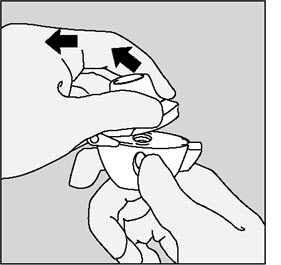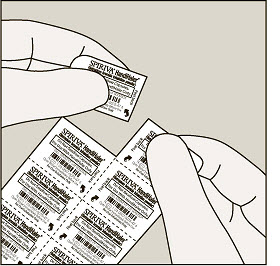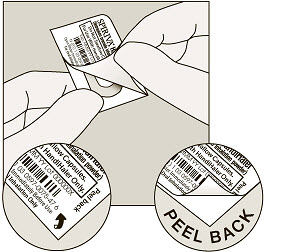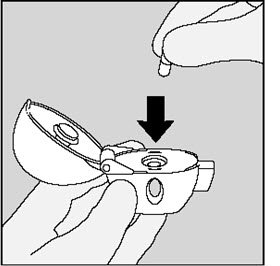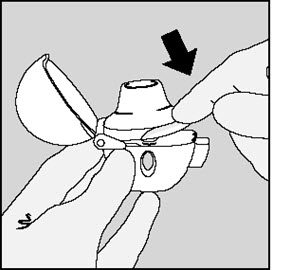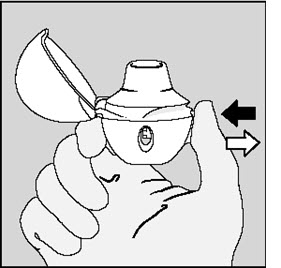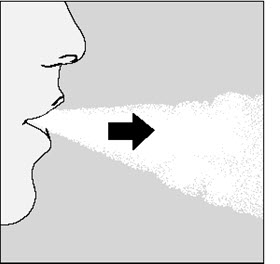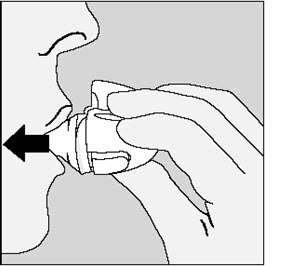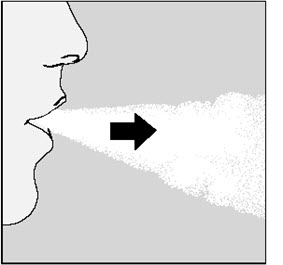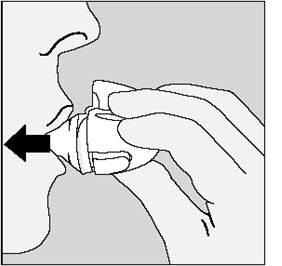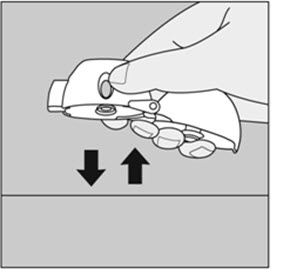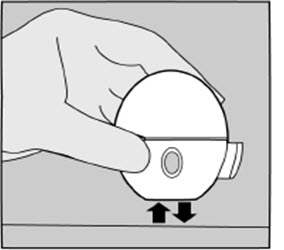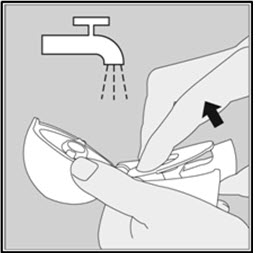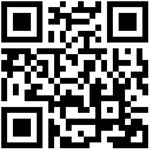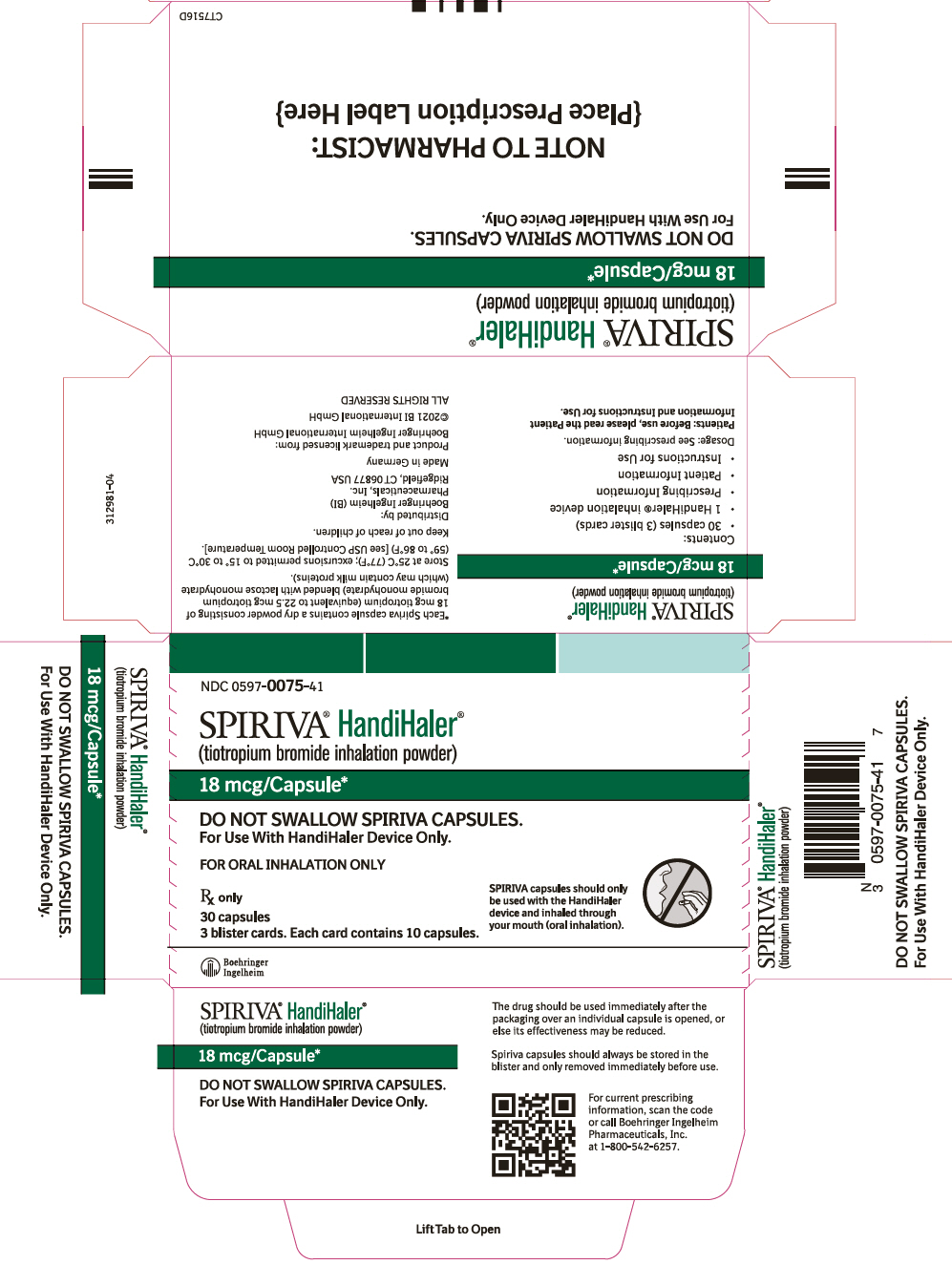 DRUG LABEL: Spiriva
NDC: 0597-0075 | Form: CAPSULE
Manufacturer: Boehringer Ingelheim Pharmaceuticals, Inc.
Category: prescription | Type: HUMAN PRESCRIPTION DRUG LABEL
Date: 20251110

ACTIVE INGREDIENTS: TIOTROPIUM BROMIDE MONOHYDRATE 18 ug/1 1

HIGHLIGHTS OF PRESCRIBING INFORMATION

These highlights do not include all the information needed to use SPIRIVA HANDIHALER safely and effectively. See full prescribing information for SPIRIVA HANDIHALER.
SPIRIVA® HANDIHALER® (tiotropium bromide inhalation powder), for oral inhalation use
Initial U.S. Approval: 2004

1 INDICATIONS AND USAGE

SPIRIVA HANDIHALER is an anticholinergic indicated for the long-term, once-daily, maintenance treatment of bronchospasm associated with chronic obstructive pulmonary disease (COPD), and for reducing COPD exacerbations (1)

2 DOSAGE AND ADMINISTRATION

- For oral inhalation only. DO NOT swallow SPIRIVA capsules. Only use SPIRIVA capsules with the HANDIHALER device (2)
- Two inhalations of the powder contents of a single SPIRIVA capsule (18 mcg) once daily (2)

3 DOSAGE FORMS AND STRENGTHS

Inhalation powder: SPIRIVA capsules contain 18 mcg tiotropium powder (equivalent to 22.5 mcg tiotropium bromide monohydrate) for use with HANDIHALER device (3)

4 CONTRAINDICATIONS

Hypersensitivity to tiotropium, ipratropium, or any components of SPIRIVA capsules (4)

5 WARNINGS AND PRECAUTIONS

- Not for acute use: Not a rescue medication (5.1)
- Immediate hypersensitivity reactions: Discontinue SPIRIVA HANDIHALER at once and consider alternatives if immediate hypersensitivity reactions, including angioedema, urticaria, rash, bronchospasm, or anaphylaxis, occur. Use with caution in patients with severe hypersensitivity to milk proteins. (5.2)
- Paradoxical bronchospasm: Discontinue SPIRIVA HANDIHALER and consider other treatments if paradoxical bronchospasm occurs (5.3)
- Worsening of narrow-angle glaucoma may occur. Use with caution in patients with narrow-angle glaucoma and instruct patients to consult a physician immediately if this occurs. (5.4)
- Worsening of urinary retention may occur. Use with caution in patients with prostatic hyperplasia or bladder-neck obstruction and instruct patients to consult a physician immediately if this occurs. (5.5)

6 ADVERSE REACTIONS

The most common adverse reactions (>5% incidence in the 1-year placebo-controlled trials) were upper respiratory tract infection, dry mouth, sinusitis, pharyngitis, non-specific chest pain, urinary tract infection, dyspepsia, and rhinitis (6.1)

To report SUSPECTED ADVERSE REACTIONS, contact Boehringer Ingelheim Pharmaceuticals, Inc. at 1-800-542-6257 or FDA at 1-800-FDA-1088 or www.fda.gov/medwatch.

7 DRUG INTERACTIONS

Anticholinergics: May interact additively with concomitantly used anticholinergic medications. Avoid administration of SPIRIVA HANDIHALER with other anticholinergic-containing drugs. (7.2)

8 USE IN SPECIFIC POPULATIONS

Patients with moderate to severe renal impairment should be monitored closely for potential anticholinergic side effects (2, 8.6)

FULL PRESCRIBING INFORMATION

1 INDICATIONS AND USAGE

SPIRIVA HANDIHALER (tiotropium bromide inhalation powder) is indicated for the long-term, once-daily, maintenance treatment of bronchospasm associated with chronic obstructive pulmonary disease (COPD), including chronic bronchitis and emphysema. SPIRIVA HANDIHALER is indicated to reduce exacerbations in COPD patients.

2 DOSAGE AND ADMINISTRATION

For oral inhalation only. Do not swallow SPIRIVA capsules, as the intended effects on the lungs will not be obtained. The contents of the SPIRIVA capsules should only be used with the HANDIHALER device [see Overdosage (10)].

The recommended dosage of SPIRIVA HANDIHALER is two inhalations of the powder contents of one SPIRIVA capsule, once-daily, with the HANDIHALER device [see Patient Counseling Information (17)]. Do not take more than one dose in 24 hours.

For administration of SPIRIVA HANDIHALER, a SPIRIVA capsule is placed into the center chamber of the HANDIHALER device. The SPIRIVA capsule is pierced by pressing and releasing the green piercing button on the side of the HANDIHALER device. The tiotropium formulation is dispersed into the air stream when the patient inhales through the mouthpiece [see Patient Counseling Information (17)].

No dosage adjustment is required for geriatric, hepatically-impaired, or renally-impaired patients. However, patients with moderate to severe renal impairment given SPIRIVA HANDIHALER should be monitored closely for anticholinergic effects [see Warnings and Precautions (5.6), Use in Specific Populations (8.5, 8.6, 8.7), and Clinical Pharmacology (12.3)].

3 DOSAGE FORMS AND STRENGTHS

Inhalation Powder: SPIRIVA HANDIHALER consists of SPIRIVA capsules containing tiotropium powder for oral inhalation and a HANDIHALER device. SPIRIVA capsules contain 18 mcg of tiotropium (equivalent to 22.5 mcg tiotropium bromide monohydrate) in a light green, hard gelatin capsule with "TI 01" printed on one side and Boehringer Ingelheim company symbol on the other side. The HANDIHALER device is only intended for use with the SPIRIVA capsules.

4 CONTRAINDICATIONS

SPIRIVA HANDIHALER is contraindicated in patients with a hypersensitivity to tiotropium, ipratropium, or any components of this product [see Warnings and Precautions (5.2)]. In clinical trials and postmarketing experience with SPIRIVA HANDIHALER, immediate hypersensitivity reactions, including angioedema (including swelling of the lips, tongue, or throat), itching, or rash have been reported [see Warnings and Precautions (5.2)].

5 WARNINGS AND PRECAUTIONS

5.1 Not for Acute Use

SPIRIVA HANDIHALER is intended as a once-daily maintenance treatment for COPD and should not be used for relief of acute symptoms, i.e., as rescue therapy for the treatment of acute episodes of bronchospasm.

5.2 Immediate Hypersensitivity Reactions

Immediate hypersensitivity reactions, including urticaria, angioedema (including swelling of the lips, tongue, or throat), rash, bronchospasm, anaphylaxis, or itching, may occur after administration of SPIRIVA HANDIHALER. If such a reaction occurs, therapy with SPIRIVA HANDIHALER should be stopped at once and alternative treatments should be considered. Given the similar structural formula of atropine to tiotropium, patients with a history of hypersensitivity reactions to atropine or its derivatives should be closely monitored for similar hypersensitivity reactions to SPIRIVA HANDIHALER. In addition, SPIRIVA HANDIHALER should be used with caution in patients with severe hypersensitivity to milk proteins.

5.3 Paradoxical Bronchospasm

Inhaled medicines, including SPIRIVA HANDIHALER, may cause paradoxical bronchospasm. If this occurs, it should be treated immediately with an inhaled short-acting beta2-agonist such as albuterol. Treatment with SPIRIVA HANDIHALER should be stopped and other treatments considered.

5.4 Worsening of Narrow-Angle Glaucoma

SPIRIVA HANDIHALER should be used with caution in patients with narrow-angle glaucoma. Prescribers and patients should be alert for signs and symptoms of acute narrow-angle glaucoma (e.g., eye pain or discomfort, blurred vision, visual halos or colored images in association with red eyes from conjunctival congestion and corneal edema). Instruct patients to consult a physician immediately should any of these signs or symptoms develop.

5.5 Worsening of Urinary Retention

SPIRIVA HANDIHALER should be used with caution in patients with urinary retention. Prescribers and patients should be alert for signs and symptoms of urinary retention (e.g., difficulty passing urine, painful urination), especially in patients with prostatic hyperplasia or bladder-neck obstruction. Instruct patients to consult a physician immediately should any of these signs or symptoms develop.

5.6 Renal Impairment

As a predominantly renally excreted drug, patients with moderate to severe renal impairment (creatinine clearance of <60 mL/min) treated with SPIRIVA HANDIHALER should be monitored closely for anticholinergic side effects [see Clinical Pharmacology (12.3)].

6 ADVERSE REACTIONS

The following adverse reactions are described, or described in greater detail, in other sections:

- Immediate hypersensitivity reactions [see Warnings and Precautions (5.2)]
- Paradoxical bronchospasm [see Warnings and Precautions (5.3)]
- Worsening of narrow-angle glaucoma [see Warnings and Precautions (5.4)]
- Worsening of urinary retention [see Warnings and Precautions (5.5)]

6.1 Clinical Trials Experience

Because clinical trials are conducted under widely varying conditions, the incidence of adverse reactions observed in the clinical trials of a drug cannot be directly compared to the incidences in the clinical trials of another drug and may not reflect the incidences observed in practice.

6-Month to 1-Year Trials

The data described below reflect exposure to SPIRIVA HANDIHALER in 2,663 patients. SPIRIVA HANDIHALER was studied in two 1-year placebo-controlled trials, two 1-year active-controlled trials, and two 6-month placebo-controlled trials in patients with COPD. In these trials, 1,308 patients were treated with SPIRIVA HANDIHALER at the recommended dosage of 18 mcg once a day. The population had an age ranging from 39 to 87 years with 65% to 85% males, 95% Caucasian, and had COPD with a mean pre-bronchodilator forced expiratory volume in one second (FEV1) percent predicted of 39% to 43%. Patients with narrow-angle glaucoma, or symptomatic prostatic hypertrophy or bladder outlet obstruction were excluded from these trials. An additional 6-month trial conducted in a Veteran's Affairs setting is not included in this safety database because only serious adverse events were collected.

The most commonly reported adverse drug reaction was dry mouth. Dry mouth was usually mild and often resolved during continued treatment. Other reactions reported in individual patients and consistent with possible anticholinergic effects included constipation, tachycardia, blurred vision, glaucoma (new onset or worsening), dysuria, and urinary retention.

Four multicenter, 1-year, placebo-controlled and active-controlled trials evaluated SPIRIVA HANDIHALER in patients with COPD. Table 1 shows all adverse reactions that occurred with a frequency of ≥3% in the SPIRIVA HANDIHALER group in the 1-year placebo-controlled trials where the rates in the SPIRIVA HANDIHALER group exceeded placebo by ≥1%. The frequency of corresponding reactions in the ipratropium-controlled trials is included for comparison.

Table 1 Adverse Reactions (% Patients) in One-Year COPD Clinical Trials
Body System (Event) | Placebo-Controlled Trials |  | Ipratropium-Controlled Trials
 | SPIRIVA (n = 550) | Placebo (n = 371) | SPIRIVA (n = 356) | Ipratropium (n = 179)
Body as a Whole
Chest Pain (non-specific) | 7 | 5 | 5 | 2
Edema, Dependent | 5 | 4 | 3 | 5
Gastrointestinal System Disorders
Dry Mouth | 16 | 3 | 12 | 6
Dyspepsia | 6 | 5 | 1 | 1
Abdominal Pain | 5 | 3 | 6 | 6
Constipation | 4 | 2 | 1 | 1
Vomiting | 4 | 2 | 1 | 2
Musculoskeletal System
Myalgia | 4 | 3 | 4 | 3
Resistance Mechanism Disorders
Infection | 4 | 3 | 1 | 3
Moniliasis | 4 | 2 | 3 | 2
Respiratory System (Upper)
Upper Respiratory Tract Infection | 41 | 37 | 43 | 35
Sinusitis | 11 | 9 | 3 | 2
Pharyngitis | 9 | 7 | 7 | 3
Rhinitis | 6 | 5 | 3 | 2
Epistaxis | 4 | 2 | 1 | 1
Skin and Appendage Disorders
Rash | 4 | 2 | 2 | 2
Urinary System
Urinary Tract Infection | 7 | 5 | 4 | 2

Arthritis, coughing, and influenza-like symptoms occurred at a rate of ≥3% in the SPIRIVA HANDIHALER treatment group, but were <1% in excess of the placebo group.

Other reactions that occurred in the SPIRIVA HANDIHALER group at a frequency of 1% to 3% in the placebo-controlled trials where the rates exceeded that in the placebo group include: Body as a Whole: allergic reaction, leg pain; Central and Peripheral Nervous System: dysphonia, paresthesia; Gastrointestinal System Disorders: gastrointestinal disorder not otherwise specified (NOS), gastroesophageal reflux, stomatitis (including ulcerative stomatitis); Metabolic and Nutritional Disorders: hypercholesterolemia, hyperglycemia; Musculoskeletal System Disorders: skeletal pain; Cardiac Events: angina pectoris (including aggravated angina pectoris); Psychiatric Disorder: depression; Infections: herpes zoster; Respiratory System Disorder (Upper): laryngitis; Vision Disorder: cataract. In addition, among the adverse reactions observed in the clinical trials with an incidence of <1% were atrial fibrillation, supraventricular tachycardia, angioedema, and urinary retention.

In the 1-year trials, the incidence of dry mouth, constipation, and urinary tract infection increased with age [see Use in Specific Populations (8.5)].

Two multicenter, 6-month, controlled studies evaluated SPIRIVA HANDIHALER in patients with COPD. The adverse reactions and the incidence rates were similar to those seen in the 1-year controlled trials.

4-Year Trial

The data described below reflect exposure to SPIRIVA HANDIHALER in 5,992 COPD patients in a 4-year placebo-controlled trial. In this trial, 2,986 patients were treated with SPIRIVA HANDIHALER at the recommended dosage of 18 mcg once a day. The population had an age range from 40 to 88 years, was 75% male, 90% Caucasian, and had COPD with a mean pre-bronchodilator FEV1 percent predicted of 40%. Patients with narrow-angle glaucoma, or symptomatic prostatic hypertrophy or bladder outlet obstruction were excluded from these trials. When the adverse reactions were analyzed with a frequency of ≥3% in the SPIRIVA HANDIHALER group where the rates in the SPIRIVA HANDIHALER group exceeded placebo by ≥1%, adverse reactions included (SPIRIVA HANDIHALER, placebo): pharyngitis (12.5%, 10.8%), sinusitis (6.5%, 5.3%), headache (5.7%, 4.5%), constipation (5.1%, 3.7%), dry mouth (5.1%, 2.7%), depression (4.4%, 3.3%), insomnia (4.4%, 3.0%), and arthralgia (4.2%, 3.1%).

Additional Adverse Reactions

Other adverse reactions not previously listed that were reported more frequently in COPD patients treated with SPIRIVA HANDIHALER than placebo include: dehydration, skin ulcer, stomatitis, gingivitis, oropharyngeal candidiasis, dry skin, skin infection, and joint swelling.

6.2 Postmarketing Experience

Adverse reactions have been identified during worldwide post-approval use of SPIRIVA HANDIHALER. Because these reactions are reported voluntarily from a population of uncertain size, it is not always possible to reliably estimate their frequency or establish a causal relationship to drug exposure. These adverse reactions are: application site irritation (glossitis, mouth ulceration, and pharyngolaryngeal pain), dizziness, dysphagia, hoarseness, intestinal obstruction including ileus paralytic, intraocular pressure increased, oral candidiasis, palpitations, pruritus, tachycardia, throat irritation, and urticaria.

7 DRUG INTERACTIONS

7.1 Sympathomimetics, Methylxanthines, Steroids

SPIRIVA HANDIHALER has been used concomitantly with short-acting and long-acting sympathomimetic (beta-agonists) bronchodilators, methylxanthines, and oral and inhaled steroids without increases in adverse reactions.

7.2 Anticholinergics

There is potential for an additive interaction with concomitantly used anticholinergic medications. Therefore, avoid coadministration of SPIRIVA HANDIHALER with other anticholinergic-containing drugs as this may lead to an increase in anticholinergic adverse effects [see Warnings and Precautions (5.4, 5.5) and Adverse Reactions (6)].

8 USE IN SPECIFIC POPULATIONS

8.1 Pregnancy

Risk Summary

The limited human data with SPIRIVA HANDIHALER use during pregnancy are insufficient to inform a drug-associated risk of adverse pregnancy-related outcomes. Based on animal reproduction studies, no structural abnormalities were observed when tiotropium was administered by inhalation to pregnant rats and rabbits during the period of organogenesis at doses 790 and 8 times, respectively, the maximum recommended human daily inhalation dose (MRHDID). Increased post-implantation loss was observed in rats and rabbits administered tiotropium at maternally toxic doses 430 times and 40 times the MRHDID, respectively [see Data].

The estimated background risk of major birth defects and miscarriage for the indicated population is unknown. All pregnancies have a background risk of birth defect, loss or other adverse outcomes. In the U.S. general population, the estimated background risk of major birth defects and miscarriage in clinically recognized pregnancies is 2% to 4% and 15% to 20%, respectively.

Data

Animal Data

In 2 separate embryo-fetal development studies, pregnant rats and rabbits received tiotropium during the period of organogenesis at doses up to approximately 790 and 8 times the MRHDID, respectively (on a mcg/m^2 basis at inhalation doses of 1,471 and 7 mcg/kg/day in rats and rabbits, respectively). No evidence of structural abnormalities was observed in rats or rabbits. However, in rats, tiotropium caused fetal resorption, litter loss, decreases in the number of live pups at birth and the mean pup weights, and a delay in pup sexual maturation at tiotropium doses of approximately 40 times the MRHDID (on a mcg/m^2 basis at a maternal inhalation dose of 78 mcg/kg/day). In rabbits, tiotropium caused an increase in post-implantation loss at a tiotropium dose of approximately 430 times the MRHDID (on a mcg/m^2 basis at a maternal inhalation dose of 400 mcg/kg/day). Such effects were not observed at approximately 5 and 95 times the MRHDID, respectively (on a mcg/m^2 basis at inhalation doses of 9 and 88 mcg/kg/day in rats and rabbits, respectively).

8.2 Lactation

Risk Summary

There are no data on the presence of tiotropium in human milk, the effects on the breastfed infant, or the effects on milk production. Tiotropium is present in milk of lactating rats; however, due to species-specific differences in lactation physiology, the clinical relevance of these data are not clear [see Data]. The developmental and health benefits of breastfeeding should be considered along with the mother's clinical need for SPIRIVA HANDIHALER and any potential adverse effects on the breastfed child from SPIRIVA HANDIHALER or from the underlying maternal condition.

Data

The distribution of tiotropium bromide into milk was investigated after a single intravenous administration of 10 mg/kg to lactating rats. Tiotropium and/or its metabolites are present in the milk of lactating rats at concentrations above those in plasma.

8.4 Pediatric Use

SPIRIVA HANDIHALER is not indicated for use in children. The safety and effectiveness of SPIRIVA HANDIHALER in pediatric patients have not been established.

8.5 Geriatric Use

Based on available data, no adjustment of SPIRIVA HANDIHALER dosage in geriatric patients is warranted [see Clinical Pharmacology (12.3)].

Of the total number of patients who received SPIRIVA HANDIHALER in the 1-year clinical trials, 426 were <65 years, 375 were 65 to 74 years, and 105 were ≥75 years of age. Within each age subgroup, there were no differences between the proportion of patients with adverse events in the SPIRIVA HANDIHALER and the comparator groups for most events. Dry mouth increased with age in the SPIRIVA HANDIHALER group (differences from placebo were 9.0%, 17.1%, and 16.2% in the aforementioned age subgroups). A higher frequency of constipation and urinary tract infections with increasing age was observed in the SPIRIVA HANDIHALER group in the placebo-controlled studies. The differences from placebo for constipation were 0%, 1.8%, and 7.8% for each of the age groups. The differences from placebo for urinary tract infections were –0.6%, 4.6%, and 4.5%. No overall differences in effectiveness were observed among these groups.

8.6 Renal Impairment

Patients with moderate to severe renal impairment (creatinine clearance of <60 mL/min) treated with SPIRIVA HANDIHALER should be monitored closely for anticholinergic side effects [see Dosage and Administration (2), Warnings and Precautions (5.6), and Clinical Pharmacology (12.3)].

8.7 Hepatic Impairment

The effects of hepatic impairment on the pharmacokinetics of tiotropium were not studied.

10 OVERDOSAGE

High doses of tiotropium may lead to anticholinergic signs and symptoms. However, there were no systemic anticholinergic adverse effects following a single inhaled dose of up to 282 mcg tiotropium in 6 healthy volunteers. In a study of 12 healthy volunteers, bilateral conjunctivitis and dry mouth were seen following repeated once-daily inhalation of 141 mcg of tiotropium.

Treatment of overdosage consists of discontinuation of SPIRIVA HANDIHALER together with institution of appropriate symptomatic and/or supportive therapy.

Accidental Ingestion

Acute intoxication by inadvertent oral ingestion of SPIRIVA capsules is unlikely since it is not well-absorbed systemically.

A case of overdose has been reported from postmarketing experience. A female patient was reported to have inhaled 30 capsules over a 2.5 day period, and developed altered mental status, tremors, abdominal pain, and severe constipation. The patient was hospitalized, SPIRIVA HANDIHALER was discontinued, and the constipation was treated with an enema. The patient recovered and was discharged on the same day.

11 DESCRIPTION

SPIRIVA HANDIHALER consists of SPIRIVA capsules and a HANDIHALER device. Each light green, hard gelatin SPIRIVA capsule contains a dry powder consisting of 18 mcg tiotropium (equivalent to 22.5 mcg tiotropium bromide monohydrate) blended with lactose monohydrate (which may contain milk proteins).

The contents of SPIRIVA capsules are intended for oral inhalation only, and are intended for administration only with the HANDIHALER device.

The active component of SPIRIVA HANDIHALER is tiotropium. The drug substance, tiotropium bromide monohydrate, is an anticholinergic with specificity for muscarinic receptors. It is chemically described as (1α, 2β, 4β, 5α, 7β)-7-[(Hydroxydi-2-thienylacetyl)oxy]-9,9-dimethyl-3-oxa-9-azoniatricyclo[3.3.1.0^2,4]nonane bromide monohydrate. It is a synthetic, non-chiral, quaternary ammonium compound. Tiotropium bromide is a white or yellowish white powder. It is sparingly soluble in water and soluble in methanol.

The structural formula is:

Tiotropium bromide (monohydrate) has a molecular mass of 490.4 and a molecular formula of C19H22NO4S2Br ∙ H2O.

The HANDIHALER device is an inhalation device used to inhale the dry powder contained in the SPIRIVA capsule. The dry powder is delivered from the HANDIHALER device at flow rates as low as 20 L/min. Under standardized in vitro testing, the HANDIHALER device delivers a mean of 10.4 mcg tiotropium when tested at a flow rate of 39 L/min for 3.1 seconds (2 L total). In a study of 26 adult patients with COPD and severely compromised lung function [mean FEV1 1.02 L (range 0.45 to 2.24 L); 37.6% of predicted (range 16% to 65%)], the median peak inspiratory flow (PIF) through the HANDIHALER device was 30.0 L/min (range 20.4 to 45.6 L/min). The amount of drug delivered to the lungs will vary depending on patient factors such as inspiratory flow and peak inspiratory flow through the HANDIHALER device, which may vary from patient to patient, and may vary with the exposure time of the SPIRIVA capsule outside the blister pack.

12 CLINICAL PHARMACOLOGY

12.1 Mechanism of Action

Tiotropium is a long-acting, antimuscarinic agent, which is often referred to as an anticholinergic. It has similar affinity to the subtypes of muscarinic receptors, M1 to M5. In the airways, it exhibits pharmacological effects through inhibition of M3-receptors at the smooth muscle leading to bronchodilation. The competitive and reversible nature of antagonism was shown with human and animal origin receptors and isolated organ preparations. In preclinical in vitro as well as in vivo studies, prevention of methacholine-induced bronchoconstriction effects was dose-dependent and lasted longer than 24 hours. The bronchodilation following inhalation of tiotropium is predominantly a site-specific effect.

12.2 Pharmacodynamics

Cardiac Electrophysiology

In a multicenter, randomized, double-blind trial using tiotropium dry powder for inhalation that enrolled 198 patients with COPD, the number of subjects with changes from baseline-corrected QT interval of 30 to 60 msec was higher in the SPIRIVA HANDIHALER group as compared with placebo. This difference was apparent using both the Bazett (QTcB) [20 (20%) patients vs. 12 (12%) patients] and Fredericia (QTcF) [16 (16%) patients vs. 1 (1%) patient] corrections of QT for heart rate. No patients in either group had either QTcB or QTcF of >500 msec. Other clinical studies with SPIRIVA HANDIHALER did not detect an effect of the drug on QTc intervals.

The effect of tiotropium dry powder for inhalation on QT interval was also evaluated in a randomized, placebo- and positive-controlled crossover study in 53 healthy volunteers. Subjects received tiotropium dry powder for inhalation 18 mcg, 54 mcg (3 times the recommended dose), or placebo for 12 days. ECG assessments were performed at baseline and throughout the dosing interval following the first and last dose of study medication. Relative to placebo, the maximum mean change from baseline in study-specific QTc interval was 3.2 msec and 0.8 msec for tiotropium dry powder for inhalation 18 mcg and 54 mcg, respectively. No subject showed a new onset of QTc >500 msec or QTc changes from baseline of ≥60 msec.

12.3 Pharmacokinetics

Tiotropium is administered by dry powder inhalation. Some of the pharmacokinetic data described below were obtained with higher doses than recommended for therapy. A dedicated pharmacokinetic study in patients with COPD evaluating once-daily tiotropium delivered from the RESPIMAT inhaler (5 mcg) and as inhalation powder (18 mcg) from the HANDIHALER device resulted in a similar systemic exposure between the two products.

Absorption

Following dry powder inhalation by young healthy volunteers, the absolute bioavailability of 19.5% suggests that the fraction reaching the lung is highly bioavailable. Oral solutions of tiotropium have an absolute bioavailability of 2-3%. Food is not expected to influence the absorption of tiotropium. Maximum tiotropium plasma concentrations were observed 7 minutes after inhalation.

Distribution

Tiotropium is 72% bound to plasma protein and had a volume of distribution of 32 L/kg after intravenous administration to young healthy volunteers. Local concentrations in the lung are not known, but the mode of administration suggests substantially higher concentrations in the lung. Studies in rats have shown that tiotropium does not readily penetrate the blood-brain barrier.

Elimination

The terminal half-life of tiotropium in COPD patients following once daily inhalation of 5 mcg tiotropium was approximately 25 hours. Total clearance was 880 mL/min after intravenous administration in young healthy volunteers. After chronic once-daily dry powder inhalation by COPD patients, pharmacokinetic steady state was reached by day 7 with no accumulation thereafter.

Metabolism

The extent of metabolism is small. This is evident from a urinary excretion of 74% of unchanged substance after an intravenous dose to young healthy volunteers. Tiotropium, an ester, is nonenzymatically cleaved to the alcohol N-methylscopine and dithienylglycolic acid, neither of which binds to muscarinic receptors.

In vitro experiments with human liver microsomes and human hepatocytes suggest that a fraction of the administered dose (74% of an intravenous dose is excreted unchanged in the urine, leaving 25% for metabolism) is metabolized by cytochrome P450-dependent oxidation and subsequent glutathione conjugation to a variety of Phase II metabolites. This enzymatic pathway can be inhibited by CYP450 2D6 and 3A4 inhibitors, such as quinidine, ketoconazole, and gestodene. Thus, CYP450 2D6 and 3A4 are involved in the metabolic pathway that is responsible for the elimination of a small part of the administered dose. In vitro studies using human liver microsomes showed that tiotropium in supra-therapeutic concentrations did not inhibit CYP450 1A1, 1A2, 2B6, 2C9, 2C19, 2D6, 2E1, or 3A4.

Excretion

Intravenously administered tiotropium bromide is mainly excreted unchanged in urine (74%). After dry powder inhalation to COPD patients at steady state, urinary excretion was 7% (1.3 mcg) of the unchanged dose over 24 hours. The renal clearance of tiotropium exceeds the creatinine clearance, indicating secretion into the urine.

Specific Populations

Geriatric Patients

As expected for all predominantly renally excreted drugs, advancing age was associated with a decrease of tiotropium renal clearance (365 mL/min in COPD patients <65 years to 271 mL/min in COPD patients ≥65 years). This did not result in a corresponding increase in AUC0-6,ss and Cmax,ss values following administration via HANDIHALER device.

Renal Impairment

Following 4-week SPIRIVA HANDIHALER or SPIRIVA RESPIMAT once daily dosing in patients with COPD, mild renal impairment (creatinine clearance 60-<90 mL/min) resulted in 6-23% higher AUC0-6,ss and 6-17% higher Cmax,ss values; moderate renal impairment (creatinine clearance 30-<60 mL/min) resulted in 54-57% higher AUC0-6,ss and 15-31% higher Cmax,ss values compared to COPD patients with normal renal function (creatinine clearance ≥90 mL/min). There is insufficient data for tiotropium exposure in patients with severe renal impairment (creatinine clearance <30 mL/min) following inhalation of SPIRIVA HANDIHALER or SPIRIVA RESPIMAT. However AUC0-4 and Cmax were 94% and 52% higher, respectively, in patients with severe renal impairment following intravenous infusion of tiotropium bromide.

Hepatic Impairment

The effects of hepatic impairment on the pharmacokinetics of tiotropium were not studied.

Drug Interactions

An interaction study with tiotropium (14.4 mcg intravenous infusion over 15 minutes) and cimetidine 400 mg three times daily or ranitidine 300 mg once daily was conducted. Concomitant administration of cimetidine with tiotropium resulted in a 20% increase in the AUC0-4h, a 28% decrease in the renal clearance of tiotropium and no significant change in the Cmax and amount excreted in urine over 96 hours. Co-administration of tiotropium with ranitidine did not affect the pharmacokinetics of tiotropium.

Common concomitant medications (long-acting beta2-adrenergic agonists (LABA), inhaled corticosteroids (ICS)) used by patients with COPD were not found to alter the exposure to tiotropium.

13 NONCLINICAL TOXICOLOGY

13.1 Carcinogenesis, Mutagenesis, Impairment of Fertility

No evidence of tumorigenicity was observed in a 104-week inhalation study in rats at tiotropium doses up to 59 mcg/kg/day, in an 83-week inhalation study in female mice at doses up to 145 mcg/kg/day, and in a 101-week inhalation study in male mice at doses up to 2 mcg/kg/day. These doses correspond to approximately 30, 40, and 0.5 times the recommended human daily inhalation dose (MRHDID) on a mcg/m^2 basis, respectively.

Tiotropium bromide demonstrated no evidence of mutagenicity or clastogenicity in the following assays: the bacterial gene mutation assay, the V79 Chinese hamster cell mutagenesis assay, the chromosomal aberration assays in human lymphocytes in vitro and mouse micronucleus formation in vivo, and the unscheduled DNA synthesis in primary rat hepatocytes in vitro assay.

In rats, decreases in the number of corpora lutea and the percentage of implants were noted at inhalation tiotropium doses of 78 mcg/kg/day or greater (approximately 40 times the MRHDID on a mcg/m^2 basis). No such effects were observed at 9 mcg/kg/day (approximately 5 times the MRHDID on a mcg/m^2 basis). The fertility index, however, was not affected at inhalation doses up to 1,689 mcg/kg/day (approximately 910 times the MRHDID on a mcg/m^2 basis).

14 CLINICAL STUDIES

The SPIRIVA HANDIHALER (tiotropium bromide inhalation powder) clinical development program consisted of six Phase 3 studies in 2,663 patients with COPD (1,308 receiving SPIRIVA HANDIHALER): two 1-year, placebo-controlled studies, two 6-month, placebo-controlled studies and two 1-year, ipratropium-controlled studies. These studies enrolled patients who had a clinical diagnosis of COPD, were 40 years of age or older, had a history of smoking greater than 10 pack-years, had a forced expiratory volume in one second (FEV1) less than or equal to 60% or 65% of predicted, and a ratio of FEV1/FVC of less than or equal to 0.7.

In these studies, SPIRIVA HANDIHALER, administered once-daily in the morning, provided improvement in lung function (FEV1), with peak effect occurring within 3 hours following the first dose.

Two additional trials evaluated exacerbations: a 6-month, randomized, double-blind, placebo-controlled, multicenter clinical trial of 1,829 COPD patients in a US Veterans Affairs setting and a 4-year, randomized, double-blind, placebo-controlled, multicenter, clinical trial of 5,992 COPD patients. Long-term effects on lung function and other outcomes, were also evaluated in the 4-year multicenter trial.

6-Month to 1-Year Effects on Lung Function

In the 1-year, placebo-controlled trials, the mean improvement in FEV1 at 30 minutes was 0.13 liters (13%) with a peak improvement of 0.24 liters (24%) relative to baseline after the first dose (Day 1). Further improvements in FEV1 and forced vital capacity (FVC) were observed with pharmacodynamic steady state reached by Day 8 with once-daily treatment. The mean peak improvement in FEV1, relative to baseline, was 0.28 to 0.31 liters (28% to 31%), after 1 week (Day 8) of once-daily treatment. Improvement of lung function was maintained for 24 hours after a single dose and consistently maintained over the 1-year treatment period with no evidence of tolerance.

In the two 6-month, placebo-controlled trials, serial spirometric evaluations were performed throughout daytime hours in Trial A (12 hours) and limited to 3 hours in Trial B. The serial FEV1 values over 12 hours (Trial A) are displayed in Figure 1. These trials further support the improvement in pulmonary function (FEV1) with SPIRIVA HANDIHALER, which persisted over the spirometric observational period. Effectiveness was maintained for 24 hours after administration over the 6-month treatment period.

Figure 1 Mean FEV1 Over Time (prior to and after administration of study drug) on Days 1 and 169 for Trial A (a Six-Month Placebo-Controlled Study) [Means adjusted for center, treatment, and baseline effect. On Day 169, a total of 183 and 149 patients in the SPIRIVA HANDIHALER and placebo groups, respectively, completed the trial. The data for the remaining patients were imputed using the last observation or least favorable observation carried forward.]

Day 1

Day 169

Results of each of the 1-year ipratropium-controlled trials were similar to the results of the 1-year placebo-controlled trials. The results of one of these trials are shown in Figure 2.

Figure 2 Mean FEV1 Over Time (0 to 6 hours post-dose) on Days 1 and 92, Respectively for One of the Two Ipratropium-Controlled Studies [Means adjusted for center, treatment, and baseline effect. On Day 92 (primary endpoint), a total of 151 and 69 patients in the SPIRIVA HANDIHALER and ipratropium groups, respectively, completed through 3 months of observation. The data for the remaining patients were imputed using the last observation or least favorable observation carried forward.]

Day 1

Day 92

A randomized, placebo-controlled clinical study in 105 patients with COPD demonstrated that bronchodilation was maintained throughout the 24-hour dosing interval in comparison to placebo, regardless of whether SPIRIVA HANDIHALER was administered in the morning or in the evening.

Throughout each week of the 1-year treatment period in the two placebo-controlled trials, patients taking SPIRIVA HANDIHALER had a reduced requirement for the use of rescue short-acting beta2-agonists. Reduction in the use of rescue short-acting beta2-agonists, as compared to placebo, was demonstrated in one of the two 6-month studies.

4-Year Effects on Lung Function

A 4-year, randomized, double-blind, placebo-controlled, multicenter clinical trial involving 5,992 COPD patients was conducted to evaluate the long-term effects of SPIRIVA HANDIHALER on disease progression (rate of decline in FEV1). Patients were permitted to use all respiratory medications (including short-acting and long-acting beta-agonists, inhaled and systemic steroids, and theophyllines) other than inhaled anticholinergics. The patients were 40 to 88 years of age, 75% male, and 90% Caucasian with a diagnosis of COPD and a mean pre-bronchodilator FEV1 of 39% predicted (range = 9% to 76%) at study entry. There was no difference between the groups in either of the co-primary efficacy endpoints, yearly rate of decline in pre- and post-bronchodilator FEV1, as demonstrated by similar slopes of FEV1 decline over time (Figure 3).

SPIRIVA HANDIHALER maintained improvements in trough (pre-dose) FEV1 (adjusted means over time: 87 to 103 mL) throughout the 4 years of the study (Figure 3).

Figure 3 Trough (pre-dose) FEV1 Mean Values at Each Time Point

Repeated measure ANOVA was used to estimate means. Means are adjusted for baseline measurements. Baseline trough FEV1 (observed mean) = 1.12. Patients with ≥3 acceptable pulmonary function tests after Day 30 and non-missing baseline value were included in the analysis.

Exacerbations

The effect of SPIRIVA HANDIHALER on COPD exacerbations was evaluated in two clinical trials: a 4-year clinical trial described above and a 6-month clinical trial of 1,829 COPD patients in a Veterans Affairs setting. In the 6-month trial, COPD exacerbations were defined as a complex of respiratory symptoms (increase or new onset) of more than one of the following: cough, sputum, wheezing, dyspnea, or chest tightness with a duration of at least 3 days requiring treatment with antibiotics, systemic steroids, or hospitalization. The population had an age ranging from 40 to 90 years with 99% males, 91% Caucasian, and had COPD with a mean pre-bronchodilator FEV1 percent predicted of 36% (range = 8% to 93%). Patients were permitted to use respiratory medications (including short-acting and long-acting beta-agonists, inhaled and systemic steroids, and theophyllines) other than inhaled anticholinergics. In the 6-month trial, the co-primary endpoints were the proportion of patients with COPD exacerbation and the proportion of patients with hospitalization due to COPD exacerbation. SPIRIVA HANDIHALER significantly reduced the proportion of COPD patients who experienced exacerbations compared to placebo (27.9% vs. 32.3%, respectively; Odds Ratio (OR) (tiotropium/placebo) = 0.81; 95% CI = 0.66, 0.99; p = 0.037). The proportion of patients with hospitalization due to COPD exacerbations in patients who used SPIRIVA HANDIHALER compared to placebo was 7.0% vs. 9.5%, respectively; OR = 0.72; 95% CI = 0.51, 1.01; p = 0.056.

Exacerbations were evaluated as a secondary outcome in the 4-year multicenter trial. In this trial, COPD exacerbations were defined as an increase or new onset of more than one of the following respiratory symptoms (cough, sputum, sputum purulence, wheezing, dyspnea) with a duration of three or more days requiring treatment with antibiotics and/or systemic (oral, intramuscular, or intravenous) steroids. SPIRIVA HANDIHALER significantly reduced the risk of an exacerbation by 14% (Hazard Ratio (HR) = 0.86; 95% CI = 0.81, 0.91; p<0.001) and reduced the risk of exacerbation-related hospitalization by 14% (HR = 0.86; 95% CI = 0.78, 0.95; p<0.002) compared to placebo. The median time to first exacerbation was delayed from 12.5 months (95% CI = 11.5, 13.8) in the placebo group to 16.7 months (95% CI = 14.9, 17.9) in the SPIRIVA HANDIHALER group.

All-Cause Mortality

In the 4-year placebo-controlled lung-function trial described above, all-cause mortality compared to placebo was assessed. There were no significant differences in all-cause mortality rates between SPIRIVA HANDIHALER and placebo.

The all-cause mortality of SPIRIVA HANDIHALER was also compared to tiotropium inhalation spray 5 mcg (SPIRIVA RESPIMAT 5 mcg) in an additional long-term, randomized, double-blind, double-dummy active-controlled study with an observation period up to 3 years. All-cause mortality was similar between SPIRIVA HANDIHALER and SPIRIVA RESPIMAT.

16 HOW SUPPLIED/STORAGE AND HANDLING

SPIRIVA HANDIHALER consists of SPIRIVA capsules and the HANDIHALER device. SPIRIVA capsules contain 18 mcg of tiotropium (equivalent to 22.5 mcg tiotropium bromide monohydrate) and are light green, with the Boehringer Ingelheim company symbol on the SPIRIVA capsule cap and "TI 01" on the SPIRIVA capsule body, or vice versa.

The HANDIHALER device is gray colored with a green piercing button. It is imprinted with SPIRIVA® HANDIHALER® (tiotropium bromide inhalation powder), and the Boehringer Ingelheim company symbol. It is also imprinted to indicate that SPIRIVA® capsules should not be stored in the HANDIHALER® device and that the HANDIHALER® device is only to be used with SPIRIVA® capsules.

SPIRIVA capsules are packaged in an aluminum/aluminum blister card and joined along a perforated-cut line. SPIRIVA capsules should always be stored in the blister and only removed immediately before use. The drug should be used immediately after the packaging over an individual SPIRIVA capsule is opened.

The following packages are available:

- carton containing 5 SPIRIVA capsules (1 unit-dose blister card) and 1 HANDIHALER inhalation device (NDC 0597-0075-75) (institutional pack)
- carton containing 30 SPIRIVA capsules (3 unit-dose blister cards) and 1 HANDIHALER inhalation device (NDC 0597-0075-41)
- carton containing 90 SPIRIVA capsules (9 unit-dose blister cards) and 1 HANDIHALER inhalation device (NDC 0597-0075-47)

Keep out of reach of children. Do not get powder into eyes.

Storage

Store at 20°C to 25°C (68° to 77°F); excursions permitted to 15°C to 30°C (59°F to 86°F) [see USP Controlled Room Temperature].

The SPIRIVA capsules should not be exposed to extreme temperature or moisture. Do not store SPIRIVA capsules in the HANDIHALER device.

17 PATIENT COUNSELING INFORMATION

Advise the patient to read the FDA-approved patient labeling (Patient Information and Instructions for Use).

Not for Acute Use:

Instruct patients that SPIRIVA HANDIHALER is a once-daily maintenance bronchodilator and should not be used for immediate relief of breathing problems (i.e., as a rescue medication).

Immediate Hypersensitivity Reactions:

Inform patients that anaphylaxis, angioedema (including swelling of the lips, tongue, or throat), urticaria, rash, bronchospasm, or itching, may occur after administration of SPIRIVA HANDIHALER. Advise patient to immediately discontinue treatment and consult a physician should any of these signs or symptoms develop.

Paradoxical Bronchospasm:

Inform patients that SPIRIVA HANDIHALER can produce paradoxical bronchospasm. Advise patients that if paradoxical bronchospasm occurs, patients should discontinue SPIRIVA HANDIHALER.

Worsening of Narrow-Angle Glaucoma:

Instruct patients to be alert for signs and symptoms of narrow-angle glaucoma (e.g., eye pain or discomfort, blurred vision, visual halos or colored images in association with red eyes from conjunctival congestion and corneal edema). Instruct patients to consult a physician immediately should any of these signs and symptoms develop.

Inform patients that care must be taken not to allow the powder to enter into the eyes as this may cause blurring of vision and pupil dilation.

Since dizziness and blurred vision may occur with the use of SPIRIVA HANDIHALER, caution patients about engaging in activities such as driving a vehicle or operating appliances or machinery.

Worsening of Urinary Retention:

Instruct patients to be alert for signs and symptoms of urinary retention (e.g., difficulty passing urine, painful urination). Instruct patients to consult a physician immediately should any of these signs or symptoms develop.

Instructions for Administering SPIRIVA HANDIHALER:

Instruct patients on how to correctly administer SPIRIVA capsules using the HANDIHALER device [see Patient Counseling Information (17)]. Instruct patients that SPIRIVA capsules should only be administered via the HANDIHALER device and the HANDIHALER device should not be used for administering other medications. Remind patients that the contents of SPIRIVA capsules are for oral inhalation only and must not be swallowed.

Instruct patients always to store SPIRIVA capsules in sealed blisters and to remove only one SPIRIVA capsule immediately before use or its effectiveness may be reduced. Instruct patients to discard unused additional SPIRIVA capsules that are exposed to air (i.e., not intended for immediate use).

Distributed by:
Boehringer Ingelheim Pharmaceuticals, Inc.
Ridgefield, CT 06877 USA

Licensed from:
Boehringer Ingelheim International GmbH

Address medical inquiries to: 1-800-542-6257.

SPIRIVA® and HANDIHALER® are registered trademarks of and are used under license from Boehringer Ingelheim International GmbH.

Copyright © 2024 Boehringer Ingelheim International GmbH
ALL RIGHTS RESERVED

COL10494BL302024
SPL10495B

Patient Information

SPIRIVA® (speh REE vah) HANDIHALER®
(tiotropium bromide inhalation powder)

Do NOT swallow SPIRIVA capsules.

Important Information: Do not swallow SPIRIVA capsules. SPIRIVA capsules should only be used with the HANDIHALER device and inhaled through your mouth (oral inhalation).

Read the information that comes with your SPIRIVA HANDIHALER before you start using it and each time you refill your prescription. There may be new information. This leaflet does not take the place of talking with your doctor about your medical condition or your treatment.

What is SPIRIVA HANDIHALER?

- SPIRIVA HANDIHALER is a prescription medicine used each day (a maintenance medicine) to control symptoms of chronic obstructive pulmonary disease (COPD), including chronic bronchitis and emphysema.
- SPIRIVA HANDIHALER helps make your lungs work better for 24 hours. SPIRIVA HANDIHALER relaxes your airways and helps keep them open. You may start to feel like it is easier to breathe on the first day, but it may take longer for you to feel the full effects of the medicine. SPIRIVA HANDIHALER works best and may help make it easier to breathe when you use it every day.
- SPIRIVA HANDIHALER reduces the likelihood of flare-ups and worsening of COPD symptoms (COPD exacerbations). A COPD exacerbation is defined as an increase or new onset of more than one COPD symptom such as cough, mucus, shortness of breath, and wheezing that requires medicine beyond your rescue medicine.

SPIRIVA HANDIHALER is not a rescue medicine and should not be used for treating sudden breathing problems. Your doctor may give you other medicine to use for sudden breathing problems.

It is not known if SPIRIVA HANDIHALER is safe and effective in children.

Who should not take SPIRIVA HANDIHALER?

Do not use SPIRIVA HANDIHALER if you:

- are allergic to tiotropium, ipratropium (Atrovent®), or any of the ingredients in SPIRIVA HANDIHALER. See the end of this leaflet for a complete list of ingredients in SPIRIVA HANDIHALER.

Symptoms of a serious allergic reaction to SPIRIVA HANDIHALER may include:

- raised red patches on your skin (hives)
- itching
- rash
- swelling of the face, lips, tongue, and throat that may cause difficulty in breathing or swallowing

If you have these symptoms of an allergic reaction, stop taking SPIRIVA HANDIHALER and call your doctor right away or go to the nearest hospital emergency room.

What should I tell my doctor before using SPIRIVA HANDIHALER?

Before taking SPIRIVA HANDIHALER, tell your doctor about all your medical conditions, including if you:

- have kidney problems.
- have glaucoma. SPIRIVA HANDIHALER may make your glaucoma worse.
- have an enlarged prostate, problems passing urine, or a blockage in your bladder. SPIRIVA HANDIHALER may make these problems worse.
- are pregnant or plan to become pregnant. It is not known if SPIRIVA HANDIHALER could harm your unborn baby.
- are breast-feeding or plan to breast-feed. It is not known if SPIRIVA HANDIHALER passes into breast milk. You and your doctor will decide if SPIRIVA HANDIHALER is right for you while you breast-feed.
- have a severe allergy to milk proteins. Ask your doctor if you are not sure.

Tell your doctor about all the medicines you take, including prescription and non-prescription medicines and eye drops, vitamins, and herbal supplements. Some of your other medicines or supplements may affect the way SPIRIVA HANDIHALER works. SPIRIVA HANDIHALER is an anticholinergic medicine. You should not take other anticholinergic medicines while using SPIRIVA HANDIHALER, including ipratropium. Ask your doctor or pharmacist if you are not sure if one of your medicines is an anticholinergic.

Know the medicines you take. Keep a list of your medicines with you to show your doctor and pharmacist when you get a new medicine.

How should I take SPIRIVA HANDIHALER?

- Use SPIRIVA HANDIHALER exactly as prescribed. Use SPIRIVA HANDIHALER one time every day.
- Read the "Instructions for Use" at the end of this leaflet before you use SPIRIVA HANDIHALER. Talk with your doctor if you do not understand the instructions.
- Do not swallow SPIRIVA capsules.
- Only use SPIRIVA capsules with the HANDIHALER device.
- Do not use the HANDIHALER device to take any other medicine.
- SPIRIVA HANDIHALER comes as a powder in a SPIRIVA capsule that fits the HANDIHALER device. Each SPIRIVA capsule, containing only a small amount of SPIRIVA powder, is one full dose of medicine.
- Separate one blister from the blister card. Then take out one of the SPIRIVA capsules from the blister package right before you use it.
- After the capsule is pierced, take a complete dose of SPIRIVA HANDIHALER by breathing in the powder by mouth two times, using the HANDIHALER device (take 2 inhalations from one SPIRIVA capsule). See the "Instructions for Use" at the end of this leaflet.
- Throw away any SPIRIVA capsule that is not used right away after it is taken out of the blister package. Do not leave the SPIRIVA capsules open to air; they may not work as well.
- If you miss a dose, take it as soon as you remember. Do not use SPIRIVA HANDIHALER more than one time every 24 hours.
- If you use more than your prescribed dose of SPIRIVA HANDIHALER, call your doctor or a poison control center.

What should I avoid while using SPIRIVA HANDIHALER?

- Do not let the powder from the SPIRIVA capsule get into your eyes. Your vision may get blurry and the pupil in your eye may get larger (dilate). If this happens, call your doctor.
- SPIRIVA HANDIHALER can cause dizziness and blurred vision. Should you experience these symptoms you should use caution when engaging in activities such as driving a car or operating appliances or other machines.

What are the possible side effects of SPIRIVA HANDIHALER?

SPIRIVA HANDIHALER can cause serious side effects, including: Allergic reaction. Symptoms may include:

- raised red patches on your skin (hives)
- itching
- rash
- swelling of the lips, tongue, or throat that may cause difficulty in breathing or swallowing

If you have these symptoms of an allergic reaction, stop taking SPIRIVA HANDIHALER and call your doctor right away or go to the nearest hospital emergency room.

- Sudden narrowing and blockage of the airways into the lungs (bronchospasm). Your breathing suddenly gets worse.

If you have these symptoms of bronchospasm, stop taking SPIRIVA HANDIHALER and call your doctor right away or go to the nearest hospital emergency room.

- New or worsened increased pressure in the eyes (acute narrow-angle glaucoma). Symptoms of acute narrow-angle glaucoma may include:
  - eye pain
  - blurred vision
  - seeing halos (visual halos) or colored images along with red eyes

Using only eye drops to treat these symptoms may not work. If you have these symptoms, stop taking SPIRIVA HANDIHALER and call your doctor right away.

- New or worsened urinary retention. Symptoms of blockage in your bladder and/or enlarged prostate may include: difficulty passing urine, painful urination.

If you have these symptoms of urinary retention, stop taking SPIRIVA HANDIHALER and call your doctor right away.

Other side effects with SPIRIVA HANDIHALER include:

- upper respiratory tract infection
- dry mouth
- sinus infection
- sore throat
- non-specific chest pain
- urinary tract infection
- indigestion
- runny nose
- constipation
- increased heart rate
- blurred vision

These are not all the possible side effects with SPIRIVA HANDIHALER. Tell your doctor if you have any side effect that bothers you or that does not go away.

Call your doctor for medical advice about side effects. You may report side effects to FDA at 1-800-FDA-1088.

How do I store SPIRIVA HANDIHALER?

- Do not store SPIRIVA capsules in the HANDIHALER device.
- Store SPIRIVA capsules in the sealed blister package at room temperature 68°F to 77°F (20°C to 25°C).
- Keep SPIRIVA capsules away from heat and cold (do not freeze).
- Store SPIRIVA capsules in a dry place. Throw away any unused SPIRIVA capsules that have been open to air.

Ask your doctor or pharmacist if you have any questions about storing your SPIRIVA capsules.

Keep SPIRIVA HANDIHALER, SPIRIVA capsules, and all medicines out of the reach of children.

General information about SPIRIVA HANDIHALER

Medicines are sometimes prescribed for purposes other than those listed in Patient Information leaflets. Do not use SPIRIVA HANDIHALER for a purpose for which it has not been prescribed. Do not give SPIRIVA HANDIHALER to other people even if they have the same symptoms that you have. It may harm them.

For more information about SPIRIVA HANDIHALER, talk with your doctor. You can ask your doctor or pharmacist for information about SPIRIVA HANDIHALER that is written for health professionals.

For current prescribing information for SPIRIVA HANDIHALER, scan the code or for additional information you may also call Boehringer Ingelheim Pharmaceuticals, Inc., at 1-800-542-6257.

What are the ingredients in SPIRIVA HANDIHALER?

Active ingredient: tiotropium
Inactive ingredient: lactose monohydrate

What is COPD (Chronic Obstructive Pulmonary Disease)?

COPD is a serious lung disease that includes chronic bronchitis, emphysema, or both. Most COPD is caused by smoking. When you have COPD, your airways become narrow. So, air moves out of your lungs more slowly. This makes it hard to breathe.

This Patient Information has been approved by the U.S. Food and Drug Administration.

Distributed by:
Boehringer Ingelheim Pharmaceuticals, Inc.
Ridgefield, CT 06877 USA

Licensed from:
Boehringer Ingelheim International GmbH

SPIRIVA® and HANDIHALER® are registered trademarks of and are used under license from Boehringer Ingelheim International GmbH.

Copyright © 2024 Boehringer Ingelheim International GmbH
ALL RIGHTS RESERVED

Revised: December 2024

COL10494BL302024
SPL10495B

Instructions for Use

SPIRIVA® (speh REE vah) HANDIHALER®
(tiotropium bromide inhalation powder)

Do not swallow SPIRIVA capsules.

Important Information about using your SPIRIVA HANDIHALER

- Do not swallow SPIRIVA capsules.
- SPIRIVA capsules should only be used with the HANDIHALER device and inhaled through your mouth (oral inhalation).
- Do not use your HANDIHALER device to take any other medicine.

First read the Patient Information, then read these Instructions for Use before you start to use SPIRIVA HANDIHALER and each time you refill your prescription. There may be new information.

Becoming familiar with your HANDIHALER device and SPIRIVA capsules:

Your SPIRIVA HANDIHALER comes with SPIRIVA capsules in blister packaging and a HANDIHALER device. Use the new HANDIHALER device provided with your medicine.

Figure A

The parts of your HANDIHALER device include:
(See Figure A)

1. dust cap (lid)
2. mouthpiece
3. mouthpiece ridge
4. base
5. green piercing button
6. center chamber
7. air intake vents

Figure B

Each SPIRIVA capsule is packaged in a blister. (See Figure B)

Figure C

- Each SPIRIVA capsule contains only a small amount of powder. (See Figure C) This is 1 full dose.
- Do not open the SPIRIVA capsule or it may not work.

Taking your full daily dose of medicine requires 4 main steps.

Step 1. Opening your HANDIHALER device:

Figure D

After removing your HANDIHALER device from the pouch:

- Open the dust cap (lid) by pressing the green piercing button. (See Figure D)

Figure E

- Pull the dust cap (lid) upwards away from the base to expose the mouthpiece. (See Figure E)

Figure F

- Open the mouthpiece by pulling the mouthpiece ridge up and away from the base so the center chamber is showing. (See Figure F)

Step 2. Inserting the SPIRIVA capsule into your HANDIHALER device:

Figure G

Each day, separate only 1 of the blisters from the blister card by tearing along the perforated line. (See Figure G)

Figure H

Remove the SPIRIVA capsule from the blister:

- Do not cut the foil or use sharp instruments to take out the SPIRIVA capsule from the blister.
- Bend 1 of the blister corners with an arrow and separate the aluminum foil layers.
- Peel back the printed foil until you see the whole SPIRIVA capsule. (See Figure H)
- If you have opened more than 1 blister to the air, the extra SPIRIVA capsule should not be used and should be thrown away.

Figure I

Place the SPIRIVA capsule in the center chamber of your HANDIHALER device. (See Figure I)

Figure J

Close the mouthpiece firmly against the gray base until you hear a click. Leave the dust cap (lid) open. (See Figure J)

Step 3. Piercing the SPIRIVA capsule:

Figure K

- Hold your HANDIHALER device with the mouthpiece pointed up. (See Figure K)
- Press the green piercing button once until it is flat (flush) against the base, then release. This is how you make holes in the SPIRIVA capsule so that you get your medicine when you breathe in.
- Do not press the green button more than one time.
- Do not shake your HANDIHALER device.
- The piercing of the SPIRIVA capsule may produce small gelatin pieces. Some of these small pieces may pass through the screen of your HANDIHALER device into your mouth or throat when you breathe in your medicine. This is normal. The small pieces of gelatin should not harm you.

Step 4. Taking your full daily dose (2 inhalations from the same SPIRIVA capsule):

Figure L

Breathe out completely in 1 breath, emptying your lungs of any air. (See Figure L)
Important: Do not breathe into your HANDIHALER device.

Figure M

With your next breath, take your medicine:

- Hold your head in an upright position while you are looking straight ahead. (See Figure M)
- Raise your HANDIHALER device to your mouth in a horizontal position. Do not block the air intake vents.
- Close your lips tightly around the mouthpiece.
- Breathe in deeply until your lungs are full. You should hear or feel the SPIRIVA capsule vibrate (rattle). (See Figure M)
- Hold your breath for a few seconds and, at the same time, take your HANDIHALER device out of your mouth.
- Breathe normally again.

The rattle tells you that you breathed in correctly. If you do not hear or feel a rattle, see the section, "If you do not hear or feel the SPIRIVA capsule rattle as you breathe in your medicine."

Figure N

To get your full daily dose, you must again, breathe out completely (See Figure N) and for a second time, breathe in (See Figure O) from the same SPIRIVA capsule.
Important: Do not press the green piercing button again.

Figure O

Remember: To get your full medicine dose each day, you must breathe in 2 times from the same SPIRIVA capsule. Make sure you breathe out completely each time before you breathe in from your HANDIHALER device.

Caring for and storing your SPIRIVA HANDIHALER:

Figure P

- After taking your daily dose, open the mouthpiece and tip out the used SPIRIVA capsule into your trash can, without touching it.
- Remove any SPIRIVA capsule pieces or SPIRIVA powder buildup by turning your HANDIHALER device upside down and gently, but firmly, tapping it. (See Figure P) Then, close the mouthpiece and dustcap for storage.
- Do not store your HANDIHALER device and SPIRIVA capsules (blisters) in a damp moist place. Always store SPIRIVA capsules in the sealed blisters.

If you do not hear or feel the SPIRIVA capsule rattle as you breathe in your medicine:

Figure Q

Do not press the green piercing button again.
Hold your HANDIHALER device with the mouthpiece pointed up and tap your HANDIHALER device gently on a table. (See Figure Q)
Check to see that the mouthpiece is completely closed. Breathe out completely before deeply breathing in again with the mouthpiece in your mouth. (See Figure O)
If you still do not hear or feel the SPIRIVA capsule rattle after repeating the above steps:

- Throw away the SPIRIVA capsule.
- Open the base by lifting the green piercing button and check the center chamber for pieces of the SPIRIVA capsule. SPIRIVA capsule pieces in the center chamber can cause a SPIRIVA capsule not to rattle.
- Turn your HANDIHALER device upside down and gently, but firmly, tap to remove the SPIRIVA capsule pieces. Call your doctor for instructions.

Cleaning your HANDIHALER device:

Figure R

Clean your HANDIHALER device as needed. (See Figure R)

- It takes 24 hours to air dry your HANDIHALER device after you clean it.
- Do not use cleaning agents or detergents.
- Do not place your HANDIHALER device in the dishwasher for cleaning.

Cleaning Steps:

- Open the dust cap and mouthpiece.
- Open the base by lifting the green piercing button.
- Look in the center chamber for SPIRIVA capsule pieces or powder buildup. If seen, tap out.
- Rinse your HANDIHALER device with warm water, pressing the green piercing button a few times so that the center chamber and the piercing needle is under the running water. Check that any powder buildup or SPIRIVA capsule pieces are removed.
- Dry your HANDIHALER device well by tipping the excess water out on a paper towel. Air-dry afterwards, leaving the dust cap, mouthpiece, and base open by fully spreading it out so that it dries completely.
- Do not use a hair dryer to dry your HANDIHALER device.
- Do not use your HANDIHALER device when it is wet. If needed, you may clean the outside of the mouthpiece with a clean damp cloth.

Helpful Hints to help ensure that you are properly taking your full daily dose of SPIRIVA HANDIHALER:

- Press the green piercing button 1 time; Breathe in 2 times; Breathe out completely before each of the 2 inhalations.
- Always use the new HANDIHALER device provided with your medicine.
- Keep your HANDIHALER device with the mouthpiece pointed up when pressing the green piercing button.
- Press the green piercing button 1 time to pierce the SPIRIVA capsule.
- Do not breathe out into your HANDIHALER device.
- Keep your HANDIHALER device in a horizontal position and keep your head upright, looking straight ahead, when breathing in.
- Check the center chamber of your HANDIHALER device for SPIRIVA capsule pieces or powder build-up. If pieces or powder are seen, tap out before use.
- Clean your HANDIHALER as needed and dry thoroughly.

For current prescribing information for SPIRIVA HANDIHALER, scan the code or for additional information you may also call Boehringer Ingelheim Pharmaceuticals, Inc., at 1-800-542-6257.

This Instructions for Use has been approved by the U.S. Food and Drug Administration.

Distributed by:
Boehringer Ingelheim Pharmaceuticals, Inc.
Ridgefield, CT 06877 USA

Licensed from:
Boehringer Ingelheim International GmbH

SPIRIVA® and HANDIHALER® are registered trademarks of and are used under license from Boehringer Ingelheim International GmbH.

Copyright © 2024 Boehringer Ingelheim International GmbH
ALL RIGHTS RESERVED

Revised: December 2024

COL10494BL302024
SPL10495B

PRINCIPAL DISPLAY PANEL - 30 Capsule Blister Pack Carton

NDC 0597-0075-41

SPIRIVA® HandiHaler®
(tiotropium bromide inhalation powder)

18 mcg/Capsule*

DO NOT SWALLOW SPIRIVA CAPSULES.
For Use With HandiHaler Device Only.

FOR ORAL INHALATION ONLY

Rx only
30 capsules
3 blister cards. Each card contains 10 capsules.

SPIRIVA capsules should only
be used with the HandiHaler
device and inhaled through
your mouth (oral inhalation).

Boehringer
Ingelheim